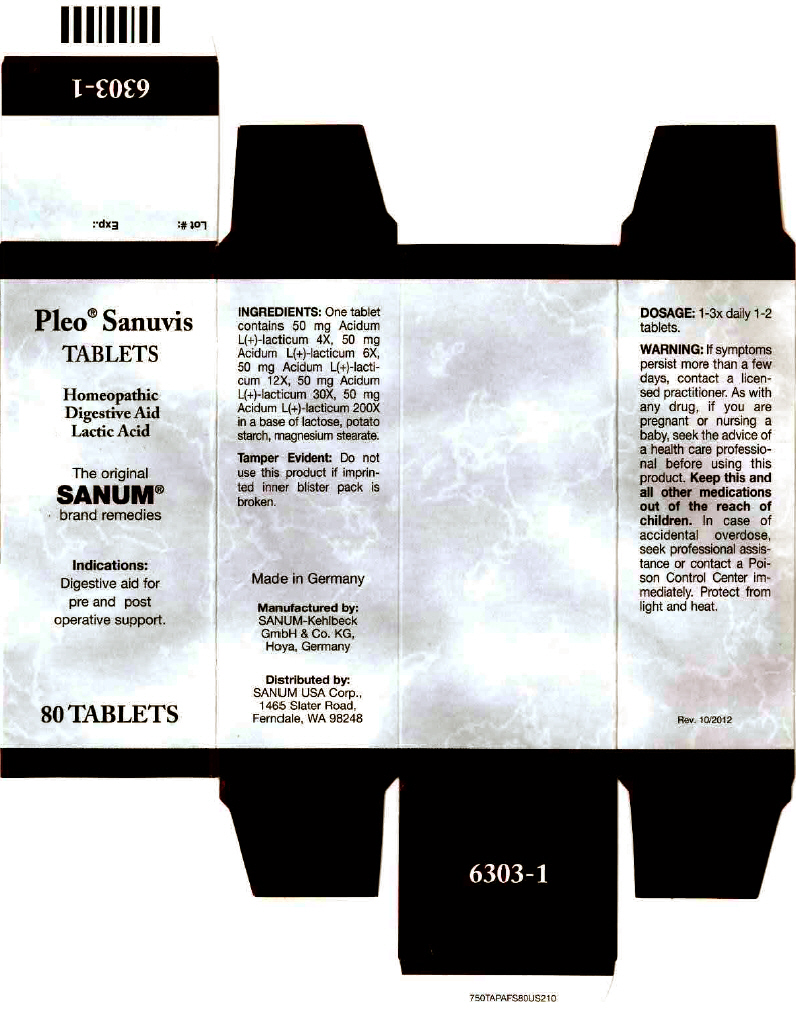 DRUG LABEL: Pleo Sanuvis
NDC: 60681-6303 | Form: TABLET
Manufacturer: Sanum Kehlbeck GmbH & Co. KG
Category: homeopathic | Type: HUMAN OTC DRUG LABEL
Date: 20130530

ACTIVE INGREDIENTS: lactic acid, l- 200 [hp_X]/1 1
INACTIVE INGREDIENTS: Lactose; Starch, Potato; Magnesium Stearate

Pleo® Sanuvis
TABLETS

PURPOSE

Homeopathic Digestive Aid Lactic Acid

80 Tablets

Indications

Digestive aid for pre and post operative support.

INGREDIENTS

INACTIVE INGREDIENT

One tablet contains 50 mg Acidum L(+)-lacticum 4X, 50 mg Acidum L(+)-lacticum 6X , 50 mg Acidum L(+)-lacticum 12X, 50 mg Acidum L(+)-lacticum 30X, 50 mg Acidum L(+)-lacticum 200X in a base of lactose, potato starch, magnesium stearate.

Tamper Evident

Do not use this product if imprinted inner blister pack is broken.

DOSAGE

1-3x daily 1-2 tablet.

WARNING

If symptoms persist more than a few days, contact a licensed practitioner. As with any drug, if you are pregnant or nursing a baby, seek the advice of a health care professional before using this product.

KEEP OUT OF REACH OF CHILDREN

Keep this and all other medications out of the reach of children. In case of accidental overdose, seek professional assistance or contact a Poison Control Center immediately.

STORAGE AND HANDLING

Protect fom light and heat.

Made in Germany

Distributed by:
SANUM USA Corp.
1465 Slater Road,
Ferndale, WA 98248

Manufactured by:
Sanum-Kehlbeck GmbH & Co. KG
Hoya, Germany

Rev. 10/2012

PRINCIPAL DISPLAY PANEL - 80 Tablet Carton

Pleo® Sanuvis
TABLETS

Homeopathic
Digestive Aid
Lactic Acid

The original
SANUM®
brand remedies

Indications:
Digestive aid for
pre and post
operative support.

80 TABLETS